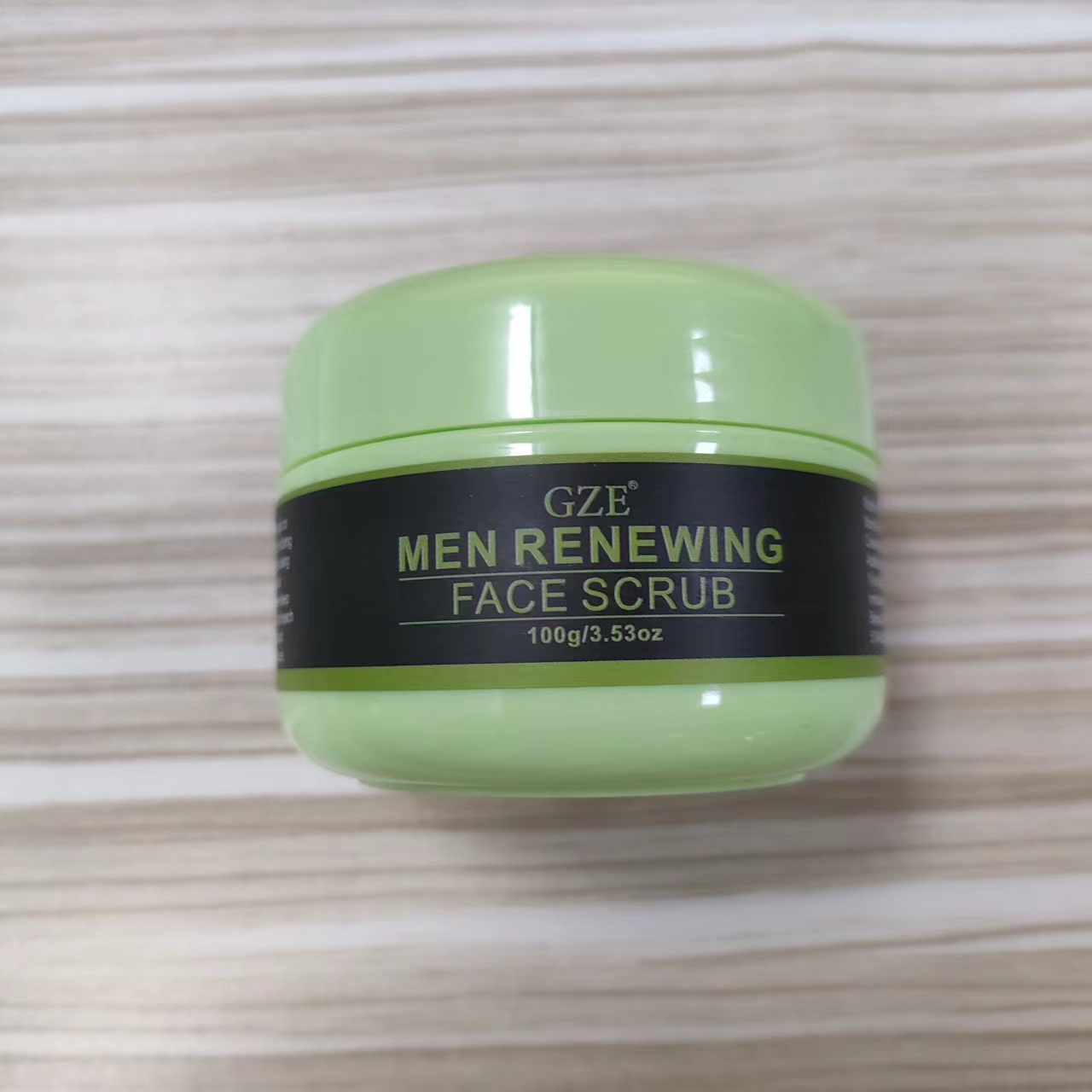 DRUG LABEL: GZE MEN RENEWING FACE SCRUB
NDC: 74458-249 | Form: GRANULE
Manufacturer: Guangzhou Yilong Cosmetics Co., Ltd
Category: otc | Type: HUMAN OTC DRUG LABEL
Date: 20241111

ACTIVE INGREDIENTS: PUMICE 10 g/100 g
INACTIVE INGREDIENTS: PERSEA GRATISSIMA (AVOCADO) OIL; HYDROLYZED JOJOBA ESTERS; TOCOPHEROL; HYDROGENATED JOJOBA OIL; ALOE BARBADENSIS LEAF EXTRACT

GZE MEN RENEWING FACE SCRUB

ACTIVE INGREDIENT

Pumice

INACTIVE INGREDIENT

Aloe Barbadensis Leaf Extract

Persea Gratissima (Avocado) Oil

Tocopherol

Hydrogenated Jojoba Oil

Jojoba Esters

PURPOSE

Exfoliation.

WARNINGS

For external use only.

INDICATIONS AND USAGE

Wash your face, take an appropriate amount of Men's Facial Scrub and apply it to your face, gently rub in a circle, and finally rinse it off with water, once a month.

Stop use and ask a doctor if rash occurs.

Do not use on damaged or broken skin.

When using this product keep out of eyes. Rinse with water to remove.

Keep out of reach of children. If swallowed, get medical help or contact a Poison Control Center right away.

DOSAGE AND ADMINISTRATION

Wash your face, take an appropriate amount of Men's Facial Scrub and apply it to your face, gently rub in a circle, and finally rinse it off with water, once a month.